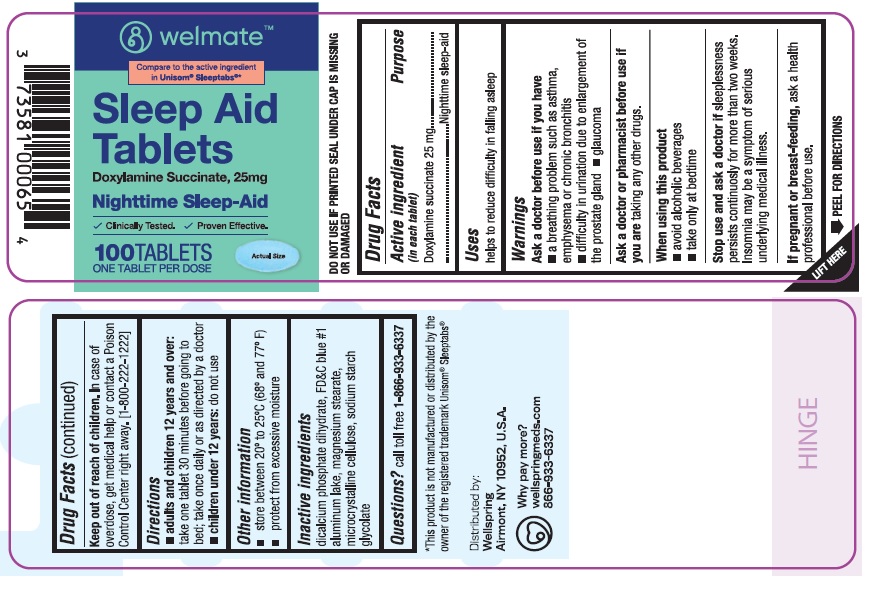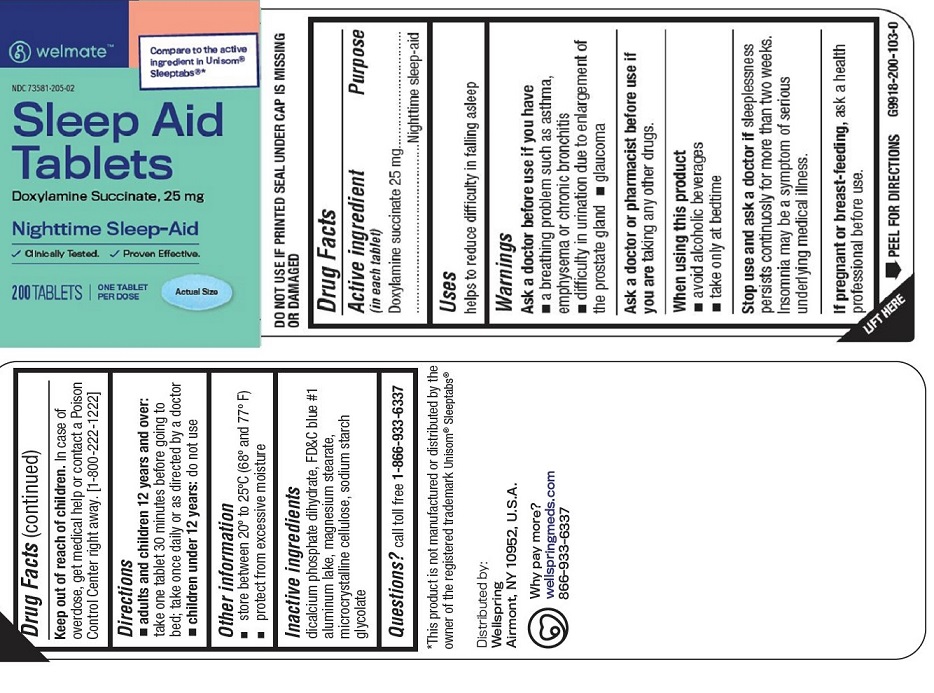 DRUG LABEL: SLEEP AID
NDC: 73581-205 | Form: TABLET
Manufacturer: YYBA CORP
Category: otc | Type: HUMAN OTC DRUG LABEL
Date: 20251202

ACTIVE INGREDIENTS: DOXYLAMINE SUCCINATE 25 mg/1 1
INACTIVE INGREDIENTS: DIBASIC CALCIUM PHOSPHATE DIHYDRATE; FD&C BLUE NO. 1 ALUMINUM LAKE; MAGNESIUM STEARATE; MICROCRYSTALLINE CELLULOSE; SODIUM STARCH GLYCOLATE TYPE A

YYBA - WELMATE - SLEEP AID TABLETS, 25 MG(73581-205)

Active ingredient (in each tablet)

Doxylamine Succinate 25 mg

Purpose

Night sleep-aid

Uses

Helps to reduce difficulty in falling asleep

Warnings

Ask a doctor before use if you have.

- a breathing problem such as asthma, emphysema or chronic bronchitis
- difficulty in urination due to enlargement of the prostate glad
- glucoma

Ask a doctor or pharmacist before use if you are taking any other drugs.

When usinf this product

- avoid alcohol beverages
- take only at bedtime

Stop use and ask a doctor if sleeplessness persists continuosly for more than two weeks. Insomnia may be s symptom of serious underlying medical illness.

If pregnant of breast-feeding, as a health professional before use.

Keep out of reach of children. In case of overdose, get medical help or contact a Poison Control Center right away [1-800-222-1222]

Directions

- adults and children 12 years and older:

take one tablet 30 minutes before going to bed; take one daily or as directed by a doctor

- children under 12 years:

do not use

Other information

- store between 20° and 25°C (68° and 77°F)
- protect from excessive moisture

Inactive ingredients

dicalcium phosphate dihydrate, FD&C blue #1 aluminum lake, magnesium stearate, microcrystalline cellulose, sodium starch glycolate

Questions?

call toll-free 1-866-933-6337